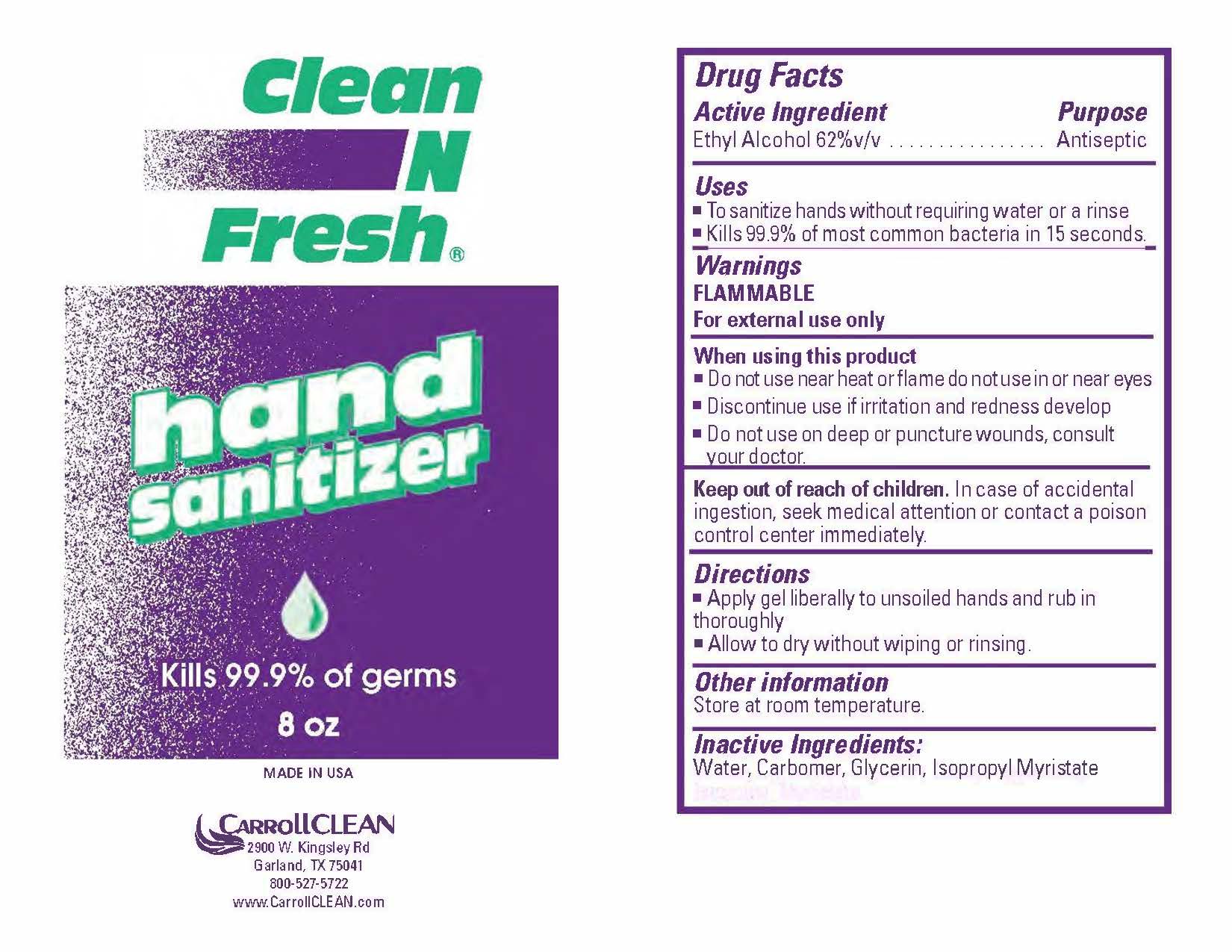 DRUG LABEL: Clean N Fresh Hand Sanitizer
NDC: 73708-515 | Form: GEL
Manufacturer: CarrollCLEAN LLC
Category: otc | Type: HUMAN OTC DRUG LABEL
Date: 20201001

ACTIVE INGREDIENTS: ALCOHOL 63.5 mL/100 mL
INACTIVE INGREDIENTS: RAPIDGEL EZ1 1.822 mL/100 mL; GLYCERIN 0.141 mL/100 mL; ISOPROPYL MYRISTATE 0.103 mL/100 mL; WATER 34.434 mL/100 mL

Clean N Fresh Hand Sanitizer

Active Ingredients

Ethyl Alcohol 62% v/v

Purpose

Antispetic

Uses

*To sanitize hands without requiring water or a rinse

*Kills 99.9% of most common bacteria in 15 seconds

Warnings

FLAMMABLE

For external use only

When using this product

*Do not use near heat or flame do not use in or near eyes

*Discontinue use if irritation and redness develop

*Do not use on deep or puncture wounds, consult your doctor.

Keep out of readh of children.

In case of accidental ingestion, seek medical attention or contact a poison control center immediately.

Directions

*Apply gel liberally to unsoiled hands and rub in thoroughly

*Allow to dry without wiping or rinsing.

Other information

Store at room temperature.

Inactive Ingredients:

Water, Carbomer, Glycerin, Isopropyl Myristate